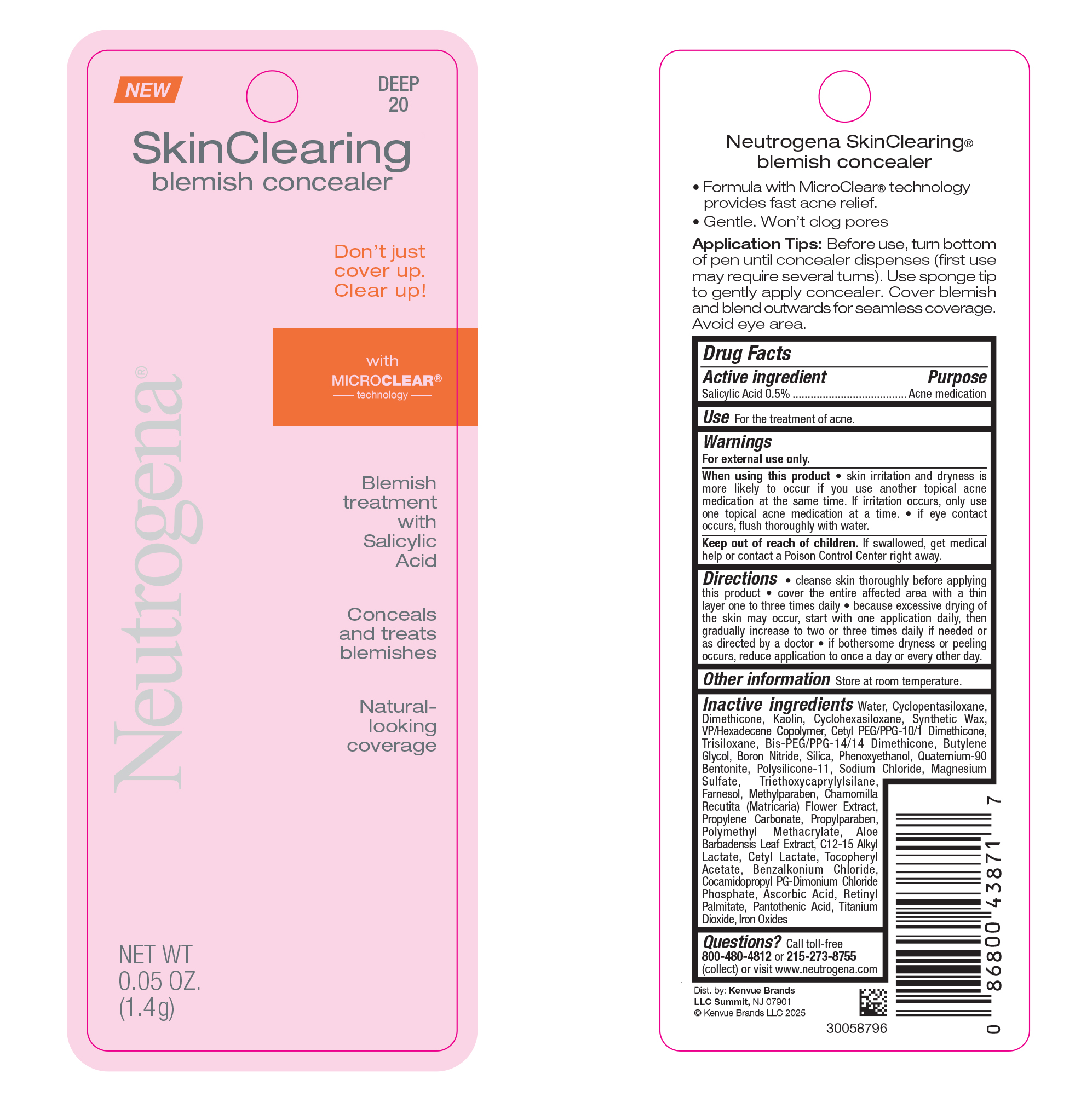 DRUG LABEL: Neutrogena
NDC: 69968-0338 | Form: LIQUID
Manufacturer: Kenvue Brands LLC
Category: otc | Type: HUMAN OTC DRUG LABEL
Date: 20250117

ACTIVE INGREDIENTS: SALICYLIC ACID 5 mg/1 g
INACTIVE INGREDIENTS: WATER; CYCLOMETHICONE 5; DIMETHICONE; KAOLIN; VINYLPYRROLIDONE/HEXADECENE COPOLYMER; TRISILOXANE; BIS-PEG/PPG-14/14 DIMETHICONE; CYCLOMETHICONE 6; BUTYLENE GLYCOL; SILICON DIOXIDE; PHENOXYETHANOL; BORON NITRIDE; DIMETHICONE/VINYL DIMETHICONE CROSSPOLYMER (SOFT PARTICLE); SODIUM CHLORIDE; MAGNESIUM SULFATE, UNSPECIFIED FORM; METHYLPARABEN; FARNESOL; CHAMOMILE; PROPYLENE CARBONATE; TRIETHOXYCAPRYLYLSILANE; PROPYLPARABEN; ALOE VERA LEAF; POLY(METHYL METHACRYLATE; 450000 MW); .ALPHA.-TOCOPHEROL ACETATE; COCAMIDOPROPYL PROPYLENE GLYCOL-DIMONIUM CHLORIDE PHOSPHATE; CETYL LACTATE; C12-15 ALKYL LACTATE; BENZALKONIUM CHLORIDE; VITAMIN A PALMITATE; PANTOTHENIC ACID; ASCORBIC ACID; TITANIUM DIOXIDE; FERRIC OXIDE RED; QUATERNIUM-90 BENTONITE; CETYL PEG/PPG-10/1 DIMETHICONE (HLB 5)

Neutrogena Skin Clearing Blemish Concealer-Deep 20

Drug Facts

Active ingredient

Salicylic Acid 0.5%

Purpose

Acne medication

Use

For the treatment of acne

Warnings

For external use only

When using this product

- skin irritation and dryness is more likely to occur if you use another topical acne medication at the same time. If irritation occurs, only use one topical acne medication at a time.

Keep out of reach of children. If swallowed, get medical help or contact a Poison Control Center right away.

Directions

- Clean the skin thoroughly before applying this product
- Cover the entire affected area with a thin layer one to three times daily
- Because excessive drying of the skin may occur, start with one application daily, then gradually increase to two or three times daily if needed or as directed by a doctor
- If bothersome dryness or peeling occurs, reduce application to once a day or every other day

Other Information

Store at room temperature

Inactive ingredients

Water, cyclopentasiloxane, dimethicone, kaolin, VP/hexadecene copolymer, synthetic wax, cetyl PEG/PPG-10/1 dimethicone, trisiloxane, BIS-PEG/PPG-14/14 dimethicone, cyclohexasiloxane, butylene glycol, silica, phenoxyethanol, boron nitride, polysilicone-11, quaternium-90 bentonite, sodium chloride, magnesium sulfate, methylparaben, farnesol, chamomilla recutita (matricaria) flower extract, propylene carbonate, triethoxycaprylylsilane, propylparaben, aloe barbadensis leaf juice, polymethyl methacrylate, tocopheryl acetate, cocamidopropyl PG-dimonium chloride phosphate, cetyl lactate, C12-15 alkyl lactate, benzalkonium chloride, retinyl palmitate, pantothenic acid, ascorbic acid,titanium dioxide, iron oxides

Questions?

Call toll-free 800-480-4812 or 215-273-8755 (collect) or visit www.neutrogena.com

Dist. by: Kenvue Brands

LLC Summit, NJ 07901

PRINCIPAL DISPLAY PANEL - 1.4 g Vial Blister Pack

NEW
DEEP
20

SkinClearing
blemish concealer
Don't just
cover up.
Clear up!
with
MICRO CLEAR®
------technology---------
Blemish
treatment
with
Salicylic
Acid

Conceals
and treats
blemishes

Natural-
looking
coverage
Neutrogena®
NET WT
0.05 OZ.
(1.4g)